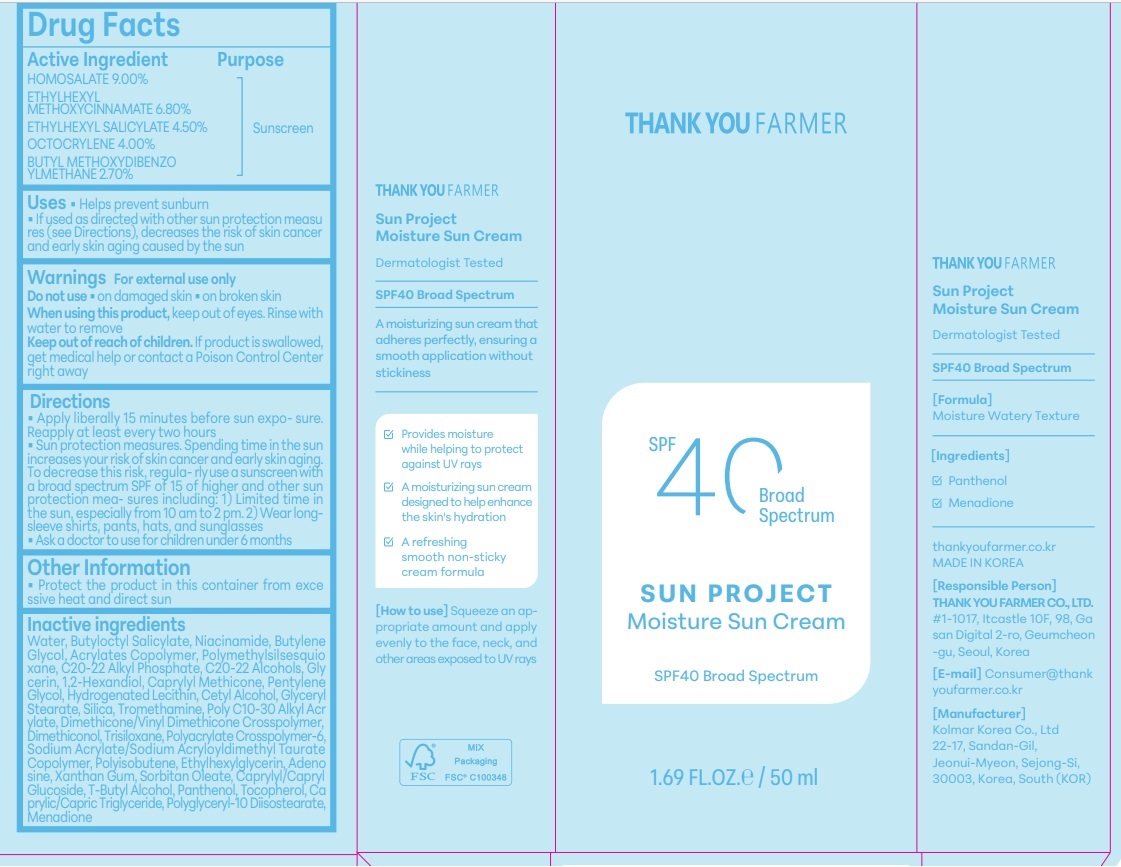 DRUG LABEL: THANKYOU FARMER Sun Project Moisture Sun
NDC: 70618-065 | Form: CREAM
Manufacturer: THANK YOU FARMER CO., LTD
Category: otc | Type: HUMAN OTC DRUG LABEL
Date: 20250313

ACTIVE INGREDIENTS: OCTINOXATE 3.4 g/50 mL; OCTISALATE 2.25 g/50 mL; HOMOSALATE 4.5 g/50 mL; OCTOCRYLENE 2 g/50 mL; AVOBENZONE 1.35 g/50 mL
INACTIVE INGREDIENTS: GLYCERIN; CAPRYLYL TRISILOXANE; SODIUM ACRYLATE/SODIUM ACRYLOYLDIMETHYLTAURATE COPOLYMER (4000000 MW); BUTYL ACRYLATE/METHYL METHACRYLATE/METHACRYLIC ACID COPOLYMER (18000 MW); TROMETHAMINE; TOCOPHEROL; NIACINAMIDE; DIMETHICONOL (100000 CST); C20-22 ALKYL PHOSPHATE; AMMONIUM ACRYLOYLDIMETHYLTAURATE; BUTYLENE GLYCOL; ADENOSINE; TERT-BUTYL ALCOHOL; WATER; C20-22 ALCOHOLS; HYDROGENATED POLYISOBUTENE (1300 MW); XANTHAN GUM; POLYGLYCERYL-10 ISOSTEARATE; 1,2-HEXANEDIOL; CETYL ALCOHOL; CAPRYLYL/CAPRYL OLIGOGLUCOSIDE; POLYMETHYLSILSESQUIOXANE (4.5 MICRONS); ETHYLHEXYLGLYCERIN; SORBITAN OLEATE DECYLGLUCOSIDE CROSSPOLYMER; HYDROGENATED SOYBEAN LECITHIN; MENADIONE; GLYCERYL STEARATE SE; DIMETHICONE/VINYL DIMETHICONE CROSSPOLYMER (SOFT PARTICLE); SILICON DIOXIDE; BUTYLOCTYL SALICYLATE; TRISILOXANE; MEDIUM-CHAIN TRIGLYCERIDES; PANTHENOL; BEHENYL ACRYLATE POLYMER; PENTYLENE GLYCOL

Active Ingredient

Active Ingredient:HOMOSALATE 9%, ETHYLHEXYL METHOXYCINNAMATE 6.8%, ETHYLHEXYL SALICYLATE 4.5%, OCTOCRYLENE 4%, BUTYL METHOXYDIBENZOYLMETHANE 2.7%

Purpose

Purpose-Sunscreen, Uses-Helps prevent sunburn

Uses

Apply Liberally 15 minutes before sun exposure. Reapply at least every two hours, Sun Protection measures. Spending time in the sun increases your risk of skin cancer and early skin aging. Decrease this risk, regularly use a sunscreen with a broad spectrum SPF of 15 of higher and other sun protection measures including: 1)Limited time in the sun, especially from 10am to 2pm. 2 sleeve shirts, pants, hats, and sunglasses. When using this product, keep eyes. with water to remove. If product is swallowed medical help or contact a Poison Control Center right away. When using this product, keep out of eyes. Rinse with water to remove.

Other Information

Other Information-Protect the product in this container from excessive heat and direct sun

Inactive Ingredients

Inactive Ingredients-WATER, BUTYLOCTYL SALICYLATE, POLYMETHYLSILSESQUIOXANE, NIACINAMIDE, BUTYLENE GLYCOL, ACRYLATES COPOLYMER, C20-22 ALKYL PHOSPHATE, C2 ALCOHOLS, GLYCERIN, 1,2-HEXANEDIOL, CAPRYLYL METHICONE, PENTYLENE GLYCOL,CETYL ALCOHOL, POLY C10-30 ALKYL ACRYLATE, TROMETHAMINE, GLYC STEARATE, SILICA, DIMETHICONE/VINYL DIMETHICONE CROSSPOLYMER, DIMETHICONOL, TRISILOXANE, POLYACRYLATE CROSSPOLYMER-6, SODIUM ACRYLATE/SODIUM ACRYLOYLDIMETHYL TAURATE COPOLYMER,POLYISOBUTENE, ETHYLHEXYLGLYCERIN, ADENOSINE, XANTHAN GUM, CAPRYLYL/CAPRYL GLUCOSIDE, SORBITAN OLEATE, T-BUTYL ALCOHOL, PANTHENOL, TOCOPHEROL, CAPRYLIC/CAPRIC TRIGLYCERIDE, POLYGLYCERYL-10 DIISOSTEARATE, HYDROGENATED LECITHIN ,MENADIONE

Dosage & administration

Dosage & administration -Apply liberally 15 minutes before sun exposure. Reapply at least every two hours

Indications & Usage

Indications & Usage Helps prevent sunburn. If used as directed with other sun protection measures (see Directions), decreases the risk of skin cancer and early skin aging caused by the sun

Keep Out Of Reach of Children- If product is swallowed, get medical help or contact a Poison Control Center right awa

Warnings

For external use only. Do not use on damaged skin & broken skin.

Ask a doctor to use for children under 6 months

PACKAGE LABEL

Package Label Principal Display Panel-Thank you Farmer, SPF40 Broad Spectrum. Sun Project Moisture Sun Cream Sunscreen, SPF40 Broad Spectrum, 1.69 FL.OZ/50ml